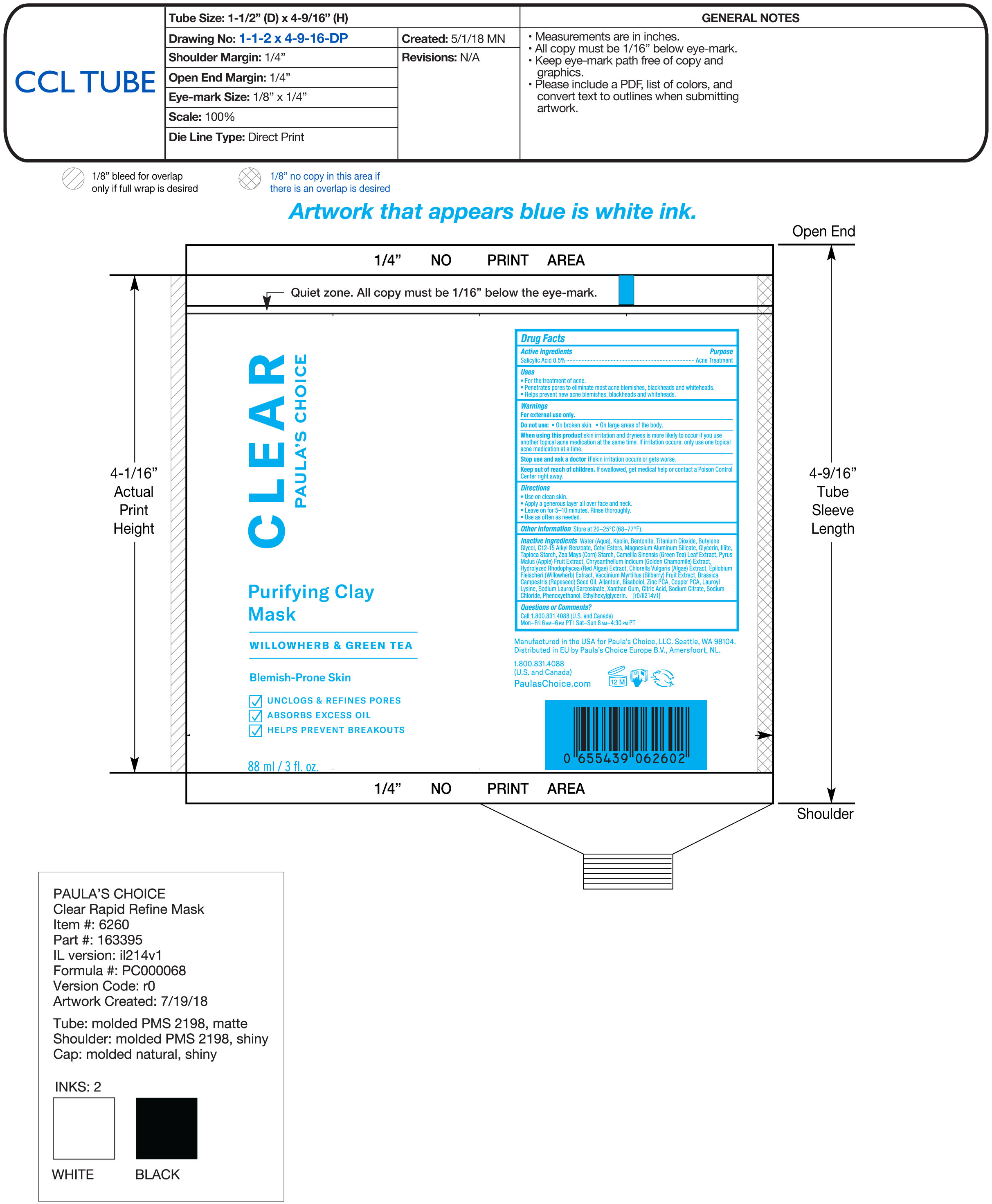 DRUG LABEL: Purifying Clay Mask
NDC: 56152-5012 | Form: CREAM
Manufacturer: Cosmetic Enterprises Ltd
Category: otc | Type: HUMAN OTC DRUG LABEL
Date: 20251014

ACTIVE INGREDIENTS: SALICYLIC ACID 0.5 g/100 mL
INACTIVE INGREDIENTS: KAOLIN; WATER; BENTONITE; CHLORELLA VULGARIS; BUTYLENE GLYCOL; ALKYL (C12-15) BENZOATE; BILBERRY; LEVOMENOL; ZINC PIDOLATE; COPPER PIDOLATE; BRASSICA RAPA SUBSP. OLEIFERA OIL; STARCH, CORN; LEDIKITE; CETYL ESTERS WAX; MAGNESIUM ALUMINUM SILICATE; GLYCERIN; TITANIUM DIOXIDE; LAUROYL LYSINE; SODIUM CITRATE; SODIUM CHLORIDE; APPLE; SODIUM LAUROYL SARCOSINATE; XANTHAN GUM; CITRIC ACID MONOHYDRATE; PHENOXYETHANOL; ETHYLHEXYLGLYCERIN; ALLANTOIN; STARCH, TAPIOCA; GREEN TEA LEAF

Purifying Clay Mask

Active Ingredients Purpose

Salicylic Acid 0.5% Acne Treatment

Uses

- For the treatment of acne
- penetrates pores to eliminate most acne blemishes, blackheads, and whiteheads
- Helps prevent new acne blemishes, blackheads and whiteheads

Keep out of reach of children.If swallowed, get medical help or contact a Poison Control Center right away.

Stop use and ask a doctorif skin irritation occurs or gets worse.

Warnings

For external use only

Do not use

- on broken skin
- on large areas of the body

When using this productskin irritation and dryness is more likely to occur if you use another topical acne medication at the same time. If irritation occurs only use one topical acne medication at a time

Directions

- Use on clean skin.
- Apply a generous layer all over face and neck.
- Leave on for 5-10 minutes. Rinse thoroughly.
- Use as often as needed.

INACTIVE INGREDIENT

Inactive ingredientsWater (Aqua), Kaolin, Bentonite, Titanium Dioxide, Butylene Glycol, C12-15 Alkyl Benzoate, Cetyl Esters, Magnesium Aluminum Silicate, Glycerin, Illite, Tapioca Starch, Zea Mays (Corn) Starch, Camellia Sinensis (Green Tea) Leaf Extract, Pyrus Malus (Apple) Fruit Extract, Chrysanthemum Indicum (Golden Chamomile) Extract, Hydrolyzed Rhodophycea (Red Algae) Extract, Chlorella Vulgaris (Algae) Extract, Epilobium Fleischeri (Willowherb) Extract, Vaccinium Myrtillus (Bilberry) Fruit Extract, Brassica Camprestris (Rapeseed) Seed Oil, Allantoin, Bisabolol, Zinc PCA, Copper PCA, Lauroyl Lysine, Sodium Lauroyl Sarcosinate, Xanthan Gum, Citric Acid, Sodium Citrate, Sodium Chloride, Phenoxyethanol, Ethylhexylglycerin

PACKAGE LABEL

Clear

Paula's Choice

Purifying Clay Mask

Willowherb & Green Tea

Blemish Prone Skin

88 ml / 3 fl. oz.